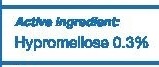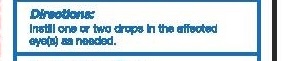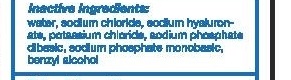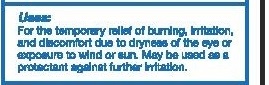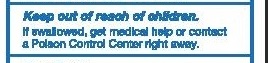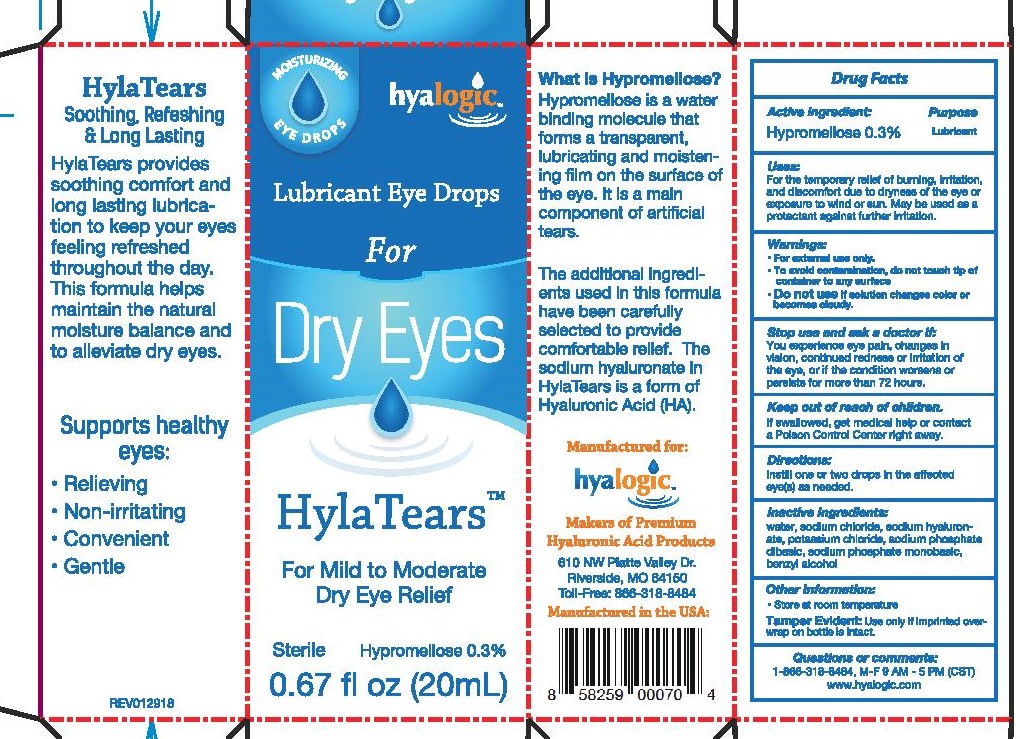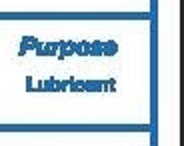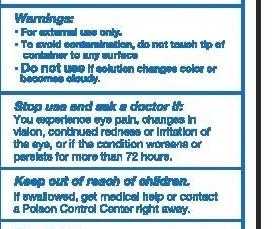 DRUG LABEL: HylaTears
NDC: 72094-001 | Form: LIQUID
Manufacturer: Hyalogic LLC
Category: otc | Type: HUMAN OTC DRUG LABEL
Date: 20250110

ACTIVE INGREDIENTS: HYPROMELLOSE 2910 (4000 MPA.S) 3 mg/10 mL
INACTIVE INGREDIENTS: POTASSIUM CHLORIDE; SODIUM PHOSPHATE DIBASIC DIHYDRATE; BENZYL ALCOHOL; WATER; SODIUM HYALURONATE; SODIUM CHLORIDE; SODIUM PHOSPHATE, MONOBASIC, UNSPECIFIED FORM

Principal display panel

Directions

Instill one or two drops in the affected eye(s) as needed.

Purpose: Lubricant

Keep out of reach of children

WARNINGS

For external use only.

If you are pregnant, nursing, trying to conceive, taking any medications, or have a medical condition, please consult your healthcare practitioner before using this product.

Stop use and ask a doctor if: You experience eye pain, changes in vision, continued redness or irritation of the eye, or if the condition worsens or persists for more than 72 hours.

Do not use if solution changes color or becomes cloudy.

If swallowed, get medical help or contact a Poison Control Center right away.

Keep out of reach of children.

Inactive Ingredients:
Water, sodium chloride, sodium hyaluron-ate, potassium chloride, sodium phosphate dibasic, sodium phosphate monobasic, benzyl alcohol.

ACTIVE INGREDIENT

Hypromellose 0.3% Lubricant

Inidication and Use

For the temporary relief of burning, irritaiton and discomofrt due to drynes of the eye or exposure to wind and sun,. May be uysed as a protectant against further irritation